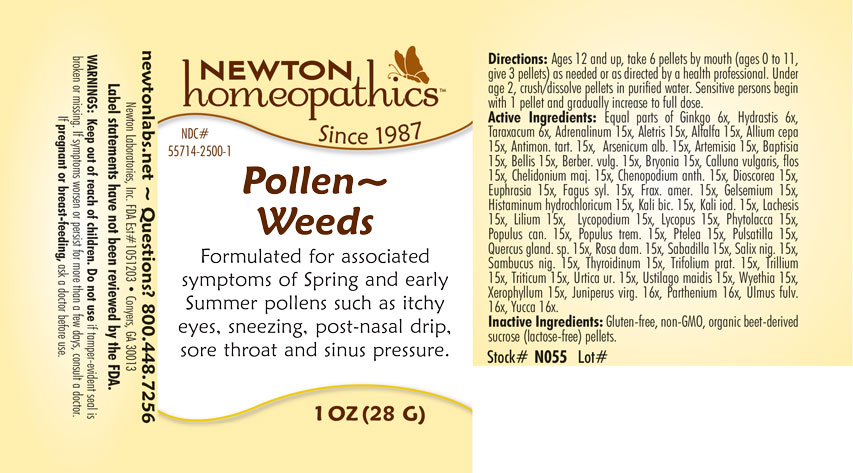 DRUG LABEL: Pollen-Weeds
NDC: 55714-2500 | Form: PELLET
Manufacturer: Newton Laboratories, Inc.
Category: homeopathic | Type: HUMAN OTC DRUG LABEL
Date: 20250207

ACTIVE INGREDIENTS: PARTHENIUM HYSTEROPHORUS 16 [hp_X]/1 g; XEROPHYLLUM ASPHODELOIDES 15 [hp_X]/1 g; ARTEMISIA VULGARIS ROOT 15 [hp_X]/1 g; EPINEPHRINE 15 [hp_X]/1 g; ALFALFA 15 [hp_X]/1 g; ALETRIS FARINOSA ROOT 15 [hp_X]/1 g; BELLIS PERENNIS 15 [hp_X]/1 g; DYSPHANIA AMBROSIOIDES 15 [hp_X]/1 g; LYCOPUS VIRGINICUS 15 [hp_X]/1 g; PHYTOLACCA AMERICANA ROOT 15 [hp_X]/1 g; POPULUS BALSAMIFERA LEAF BUD 15 [hp_X]/1 g; POPULUS TREMULOIDES LEAF 15 [hp_X]/1 g; PTELEA TRIFOLIATA BARK 15 [hp_X]/1 g; SAMBUCUS NIGRA FLOWERING TOP 15 [hp_X]/1 g; TRILLIUM ERECTUM ROOT 15 [hp_X]/1 g; ELYMUS REPENS ROOT 15 [hp_X]/1 g; URTICA URENS 15 [hp_X]/1 g; WYETHIA HELENIOIDES ROOT 15 [hp_X]/1 g; YUCCA FILAMENTOSA 16 [hp_X]/1 g; HISTAMINE DIHYDROCHLORIDE 15 [hp_X]/1 g; JUNIPERUS VIRGINIANA TWIG 16 [hp_X]/1 g; THYROID, UNSPECIFIED 15 [hp_X]/1 g; USTILAGO MAYDIS 15 [hp_X]/1 g; ONION 15 [hp_X]/1 g; ANTIMONY POTASSIUM TARTRATE 15 [hp_X]/1 g; ARSENIC TRIOXIDE 15 [hp_X]/1 g; BAPTISIA TINCTORIA ROOT 15 [hp_X]/1 g; BERBERIS VULGARIS ROOT BARK 15 [hp_X]/1 g; BRYONIA ALBA ROOT 15 [hp_X]/1 g; CHELIDONIUM MAJUS 15 [hp_X]/1 g; EUPHRASIA STRICTA 15 [hp_X]/1 g; GELSEMIUM SEMPERVIRENS ROOT 15 [hp_X]/1 g; POTASSIUM DICHROMATE 15 [hp_X]/1 g; POTASSIUM IODIDE 15 [hp_X]/1 g; LACHESIS MUTA VENOM 15 [hp_X]/1 g; LYCOPODIUM CLAVATUM SPORE 15 [hp_X]/1 g; ANEMONE PULSATILLA 15 [hp_X]/1 g; SCHOENOCAULON OFFICINALE SEED 15 [hp_X]/1 g; DIOSCOREA VILLOSA TUBER 15 [hp_X]/1 g; GINKGO 6 [hp_X]/1 g; TARAXACUM OFFICINALE 6 [hp_X]/1 g; GOLDENSEAL 6 [hp_X]/1 g; QUERCUS ROBUR NUT 15 [hp_X]/1 g; CALLUNA VULGARIS FLOWERING TOP 15 [hp_X]/1 g; ULMUS RUBRA BARK 16 [hp_X]/1 g; FAGUS SYLVATICA NUT 15 [hp_X]/1 g; TRIFOLIUM PRATENSE FLOWER 15 [hp_X]/1 g; FRAXINUS AMERICANA BARK 15 [hp_X]/1 g; LILIUM LANCIFOLIUM WHOLE FLOWERING 15 [hp_X]/1 g; ROSA DAMASCENA FLOWERING TOP 15 [hp_X]/1 g; SALIX NIGRA BARK 15 [hp_X]/1 g
INACTIVE INGREDIENTS: SUCROSE

Pollen 2500P

INDICATIONS & USAGE SECTION

Formulated for associated symptoms of Spring and early Summer pollens such as itchy eyes, sneezing, post-nasal drip, sore throat and sinus pressure.

OTC - ACTIVE INGREDIENT SECTION

Equal parts of Ginkgo biloba 6x, Hydrastis canadensis 6x, Taraxacum officinale 6x, Adrenalinum 15x, Aletris farinosa 15x, Alfalfa 15x, Allium cepa 15x, Antimonium tartaricum 15x, Arsenicum album 15x, Artemisia vulgaris 15x, Baptisia tinctoria 15x, Bellis perennis 15x, Berberis vulgaris 15x, Bryonia 15x, Calluna vulgaris, flos 15x, Chelidonium majus 15x, Chenopodium anthelminticum 15x, Dioscorea vilosa 15x, Euphrasia officinalis 15x, Fagus sylvatica 15x, Fraxinus americana 15x, Gelsemium sempervirens 15x, Histaminum hydrochloricum 15x, Kali bichromicum 15x, Kali iodatum 15x, Lachesis mutus 15x, Lilium tigrinum 15x, Lycopodium clavatum 15x, Lycopus virginicus 15x, Phytolacca decandra 15x, Populus candicans 15x, Populus tremuloides 15x, Ptelea trifoliata 15x, Pulsatilla 15x, Quercus glandium spiritus 15x, Rosa damascena 15x, Sabadilla 15x, Salix nigra 15x, Sambucus nigra 15x, Thyroidinum 15x, Trifolium pratense 15x, Trillium pendulum 15x, Triticum repens 15x, Urtica urens 15x, Ustilago maidis 15x, Wyethia helenoides 15x, Xerophyllum asphodeloides 15x, Juniperus virginiana 16x, Parthenium 16x, Ulmus fulva 16x, Yucca filamentosa 16x.

OTC - PURPOSE SECTION

Formulated for associated symptoms of Spring and early Summer pollens such as itchy eyes, sneezing, post-nasal drip, sore throat and sinus pressure.

INACTIVE INGREDIENT SECTION

Inactive Ingredients: Gluten-free, non-GMO, organie beet-derived sucrose (lactose-free) pellets.

QUESTIONS SECTION

newtonlabs.net – Questions? 800.448.7256

Newton Laboratories, Inc. FDA Est # 1051203 - Conyers, GA 30013

WARNINGS SECTION

Warnings: Keep out of reach of children. Do no use if tamper-evident seal is broken or missing. If symptoms worsen or persist for more than a few days, consult a doctor. If pregnant or breast-feeding, ask a doctor before use.

OTC - PREGNANCY OR BREAST FEEDING SECTION

If pregnant or breast-feeding, ask a doctor before use.

OTC - KEEP OUT OF REACH OF CHILDREN SECTION

Keep out of reach of children.